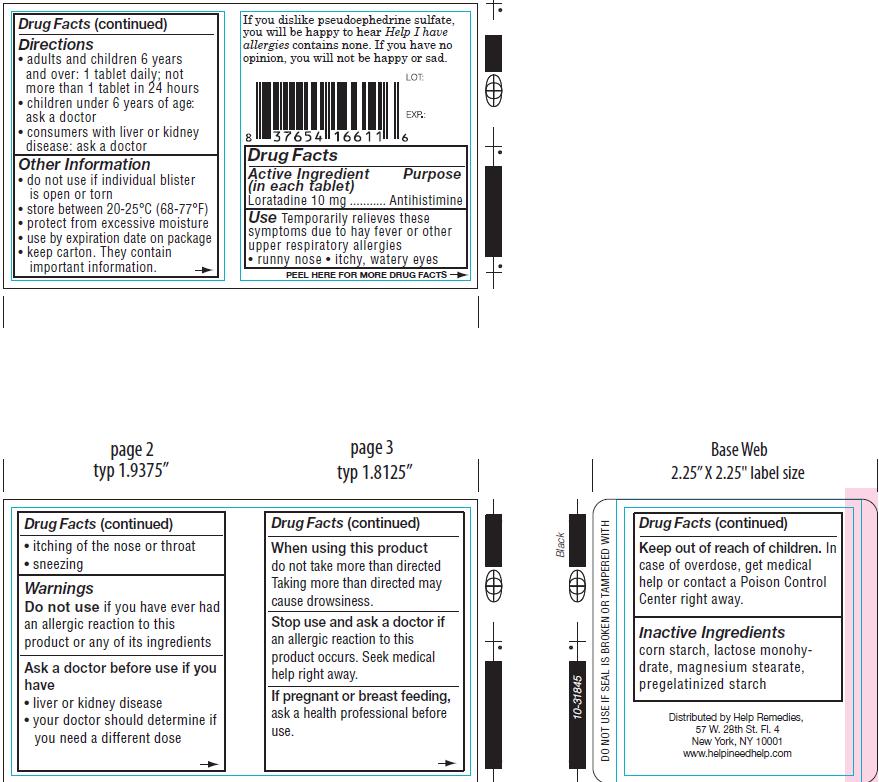 DRUG LABEL: Help I have allergies
NDC: 49260-611 | Form: TABLET
Manufacturer: Help Remedies, Inc.
Category: otc | Type: HUMAN OTC DRUG LABEL
Date: 20130306

ACTIVE INGREDIENTS: Loratadine 10 mg/1 1
INACTIVE INGREDIENTS: STARCH, CORN; LACTOSE MONOHYDRATE; MAGNESIUM STEARATE; STARCH, CORN

Drug Facts

Active Ingredient Purpose
(in each tablet)

Loratadine 10mg..........................................Antihistamine

Use

Temporarily relieves these symptoms due to hay fever or other upper respiratory allergies

- runny nose
- itchy, watery eyes
- itching of the nose or throat
- sneezing

Warnings
Do not use ifyou have ever had an allergic reaction to this product or any of its ingredients
Ask a doctor before use if you have

- liver or kidney disease
- your doctor should determine if you need a different dose

When using this product do not take more than directed.Taking more than directed may
cause drowsiness.
Stop use and ask a doctor if an allergic reaction to this product occurs. Seek medical
help right away.

Keep out of reach of children. In case of overdose, get medical help or contact a Poison Control
Center right away.

PREGNANCY OR BREAST FEEDING

If pregnant or breast feeding, ask a health professional before use.

Directions

- adults and children 6 years and over: 1 tablet daily; not more than 1 tablet in 24 hours
- children under 6 years of age: ask a doctor
- consumers with liver or kidney disease: ask a doctor

Other Information

- do not use if individual blister is open or torn
- store between 20-25 degrees celcius (68-77 degrees fahrenheits)
- protect from excessive moisture
- use by expiration date on package
- keep carton. They contain important information.

Inactive Ingredients
corn starch, lactose monohydrate, magnesium stearate,pregelatinized starch

QUESTIONS

Distributed by Help Remedies,
57 W. 28th St. Fl. 4
New York, NY 10001
www.helpineedhelp.com